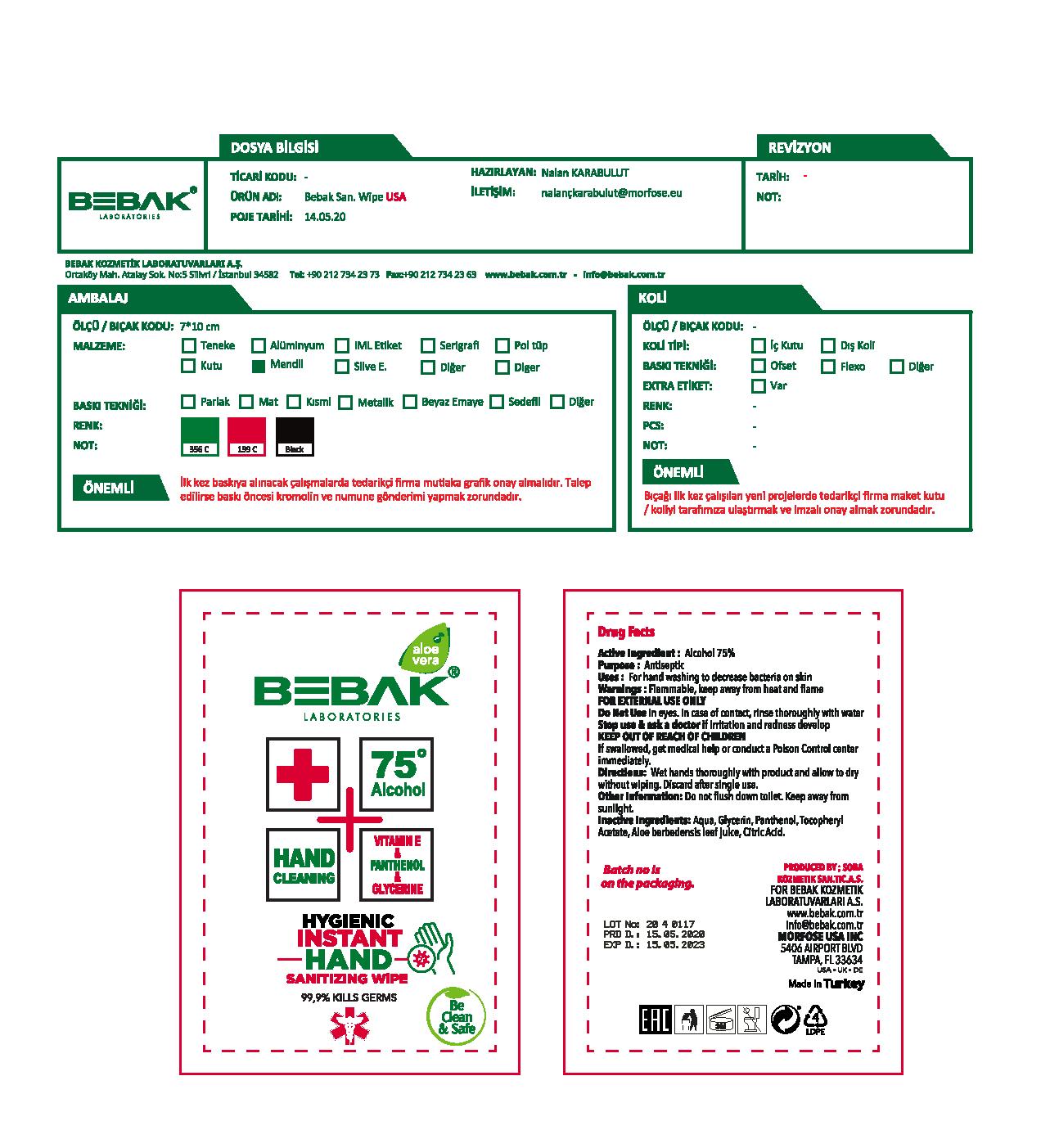 DRUG LABEL: Bebak Laboratories Hygenic Instant Hand Sanitizing Wipe
NDC: 77462-004 | Form: LIQUID
Manufacturer: SORA KOZMETIK SANAYI TICARET ANONIM SIRKETI
Category: otc | Type: HUMAN OTC DRUG LABEL
Date: 20200714

ACTIVE INGREDIENTS: ALCOHOL 75 mL/100 mL
INACTIVE INGREDIENTS: WATER; ALPHA-TOCOPHEROL ACETATE; CITRIC ACID MONOHYDRATE; ALOE VERA LEAF; GLYCERIN; PANTHENOL

Bebak Laboratories

Active Ingredient

Alcohol 75%

Purpose

Antiseptic

Uses

For hand washing to decrease bacteria on the skin.

Warnings

Flammable, keep away from fire or flame.

For external use only.

Do not use in the eyes. In case of contact rinse thoroughly with water.

Stop use and ask a doctor if

irritation and redness develop

KEEP OUT OF REACH OF CHILDREN. If swallowed, get medical help or contact a Poison Control Center right away.

Directions

Wet hands thoroughly with product and allow to dry without wiping. Discard after single use.

Other Information

Do not flush down toilet. Keep away from sunlight.

Inactive Ingredients

Aqua Glycerin, Panthenol, Tocopheryl Acetate, Aloe Barbadensis Leaf Juice, Citric Acid